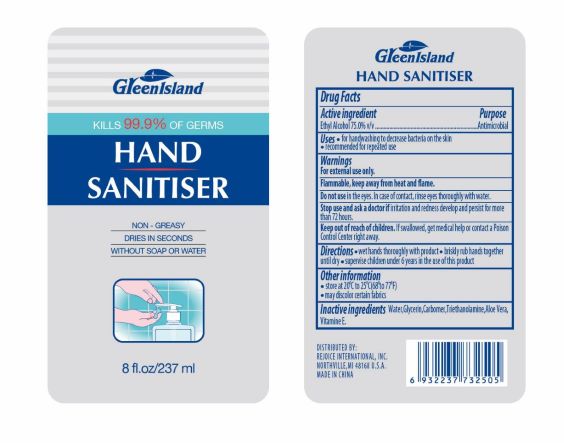 DRUG LABEL: Sani Pure Hand Sanitizer
NDC: 71712-003 | Form: GEL
Manufacturer: Wuxi Huoban Daily-Use Chemicals Science and Technology Co., Ltd
Category: otc | Type: HUMAN OTC DRUG LABEL
Date: 20200629

ACTIVE INGREDIENTS: ALCOHOL 75 mL/100 mL
INACTIVE INGREDIENTS: GLYCERIN; WATER; TROLAMINE; ALOE VERA WHOLE

Drug Facts Active Ingredients

Ethyl Alcohol 75%

Purpose

Antimicrobial

Directions:

- Wet hands thoroughly with product
- briskly rub hands together
- supervise children under 6 years in the use of this product

Inactive Ingredients:

Aqua,Glycerin, Carbomer, Triethanolamine, Aloe Vera, Vitamine E

Warning

- Flammable, keep away from flame.
- Do not use in eyes. In case of ontact immediately flush eyes with water then contact physician.
- If swallowed, get medical help or contact a Poison Control Center
- For External Use Only.

Keep out of reach of children.

OTHER SAFETY INFORMATION

- store at 20C to 25C (68 to 77F)
- may discolor certain fabrics

INDICATIONS AND USAGE

- for handwashing to decrease bacteria on the skin
- recommended for repeated use